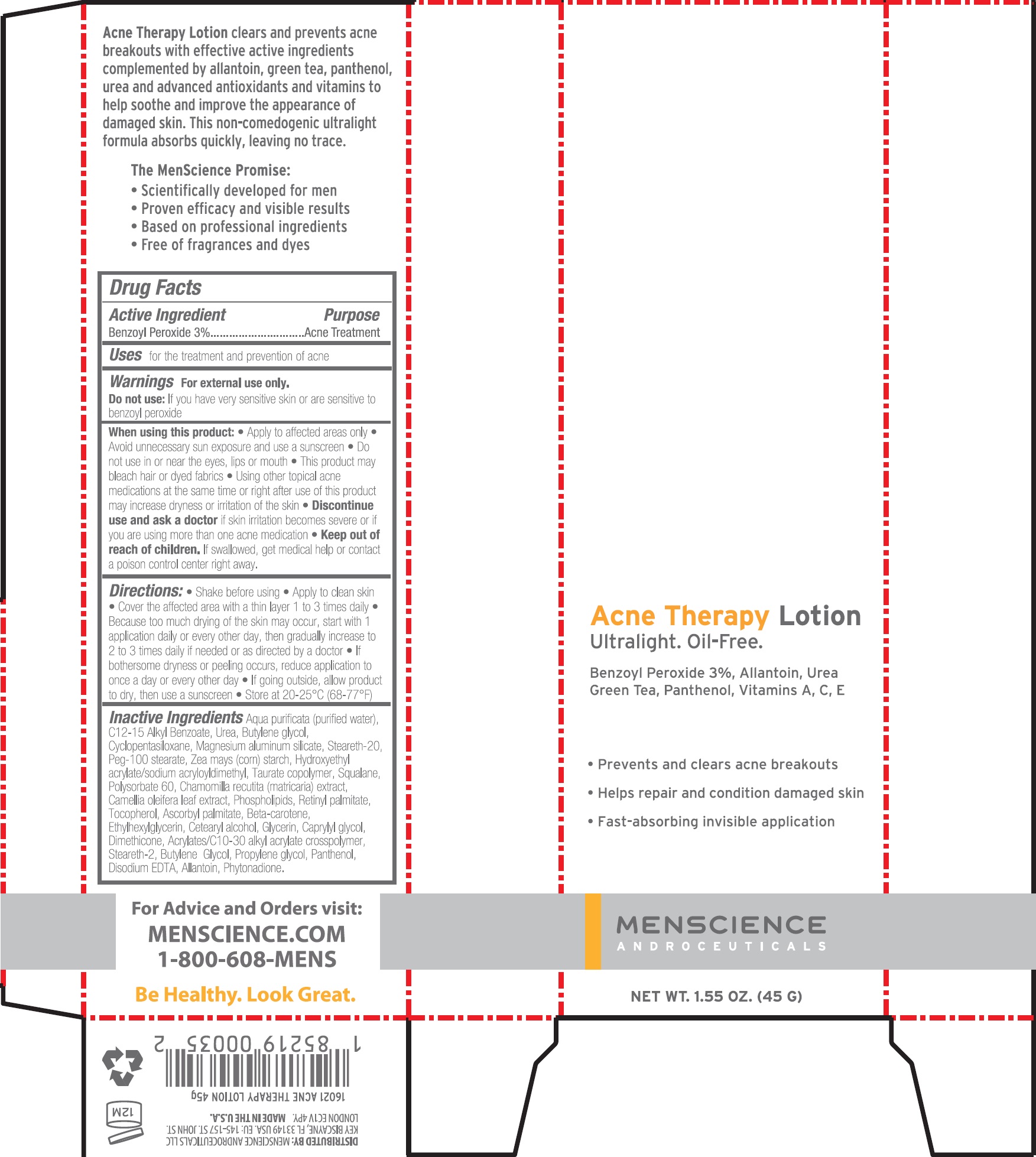 DRUG LABEL: ACNE THERAPY
NDC: 71397-822 | Form: LOTION
Manufacturer: menScience Androceuticals, LLC
Category: otc | Type: HUMAN OTC DRUG LABEL
Date: 20231111

ACTIVE INGREDIENTS: BENZOYL PEROXIDE 30 mg/1 g
INACTIVE INGREDIENTS: WATER; ALKYL (C12-15) BENZOATE; UREA; BUTYLENE GLYCOL; CYCLOMETHICONE 5; MAGNESIUM ALUMINUM SILICATE; STEARETH-20; PEG-100 STEARATE; STARCH, CORN; HYDROXYETHYL ACRYLATE/SODIUM ACRYLOYLDIMETHYL TAURATE COPOLYMER (100000 MPA.S AT 1.5%); SQUALANE; POLYSORBATE 60; MATRICARIA CHAMOMILLA; CAMELLIA OLEIFERA LEAF; LECITHIN, SOYBEAN; VITAMIN A PALMITATE; TOCOPHEROL; ASCORBYL PALMITATE; .BETA.-CAROTENE; ETHYLHEXYLGLYCERIN; CETOSTEARYL ALCOHOL; GLYCERIN; CAPRYLYL GLYCOL; DIMETHICONE; STEARETH-2; PROPYLENE GLYCOL; PANTHENOL; EDETATE DISODIUM ANHYDROUS; ALLANTOIN; PHYTONADIONE

ACNE THERAPY LOTION

Active Ingredient

Benzoyl Peroxide 3%

Purpose

Acne Treatment

Uses

for the treatment and prevention of acne

Warnings

For external use only.

Do not use:

If you have very sensitive skin or sensitive to benzoyl peroxide.

When using this product:

Apply to affected areas only. Avoid unnecessary sun exposure and use a sunscreen. Do not use in or near the eyes, lips or mouth. This product may bleach hair or dyed fabrics. Using other topical acne medications at the same time or right after use of this product may increase dryness or irritation of the skin.

Discontinue use and ask a doctor

if skin irritation becomes severe or if you are using more than one acne medication.

Keep out of reach of children.

If swallowed, get medical help or contact a poison control center right away.

Directions:

Shake before using. Apply to clean skin. Cover the affected area with a thin layer 1 to 3 times daily. Because too much drying of the skin may occur, start with 1 application daily or every other day, then gradually increase to 2 to 3 times daily if needed or as directed by a doctor. If bothersome dryness or peeling occurs, reduce applicaction once a day or every other day. If going outside, allow product to dry, then use a sunscreen. Store at 20-25 C (68-77 F)oo

Inactive Ingredients

Aqua purificata (purified water), C12-15 Alkyl Benzoate, Urea, Butylene Glycol, Cyclopentasiloxane, Magnesium aluminum silicated, Steareth-20, Peg-100 stearate, Zea mays (corn) starch, Hydroxyethyl acrylate/sodium acryloydimethyl, Taurate copolymer, Squalane, Polysorbate 60, Chamomilla recutita (matricaria) extract, Camellia oleifera leaf extract, Phospholipids, Retinyl palmitate, Tocopherol, Ascorbyl palmitate, Beta-carotene, Ethylhexylglycerin, Cetearyl alcohol, Glycerin, Caprylyl glycol, Dimethicone, Acrylates/C10-30 alkyl acrylate crosspolymer, Steareth-2, Butylene Glycol, Propylene glycol, Panthenol, Disodium EDTA, Allantoin, Phytonadione.